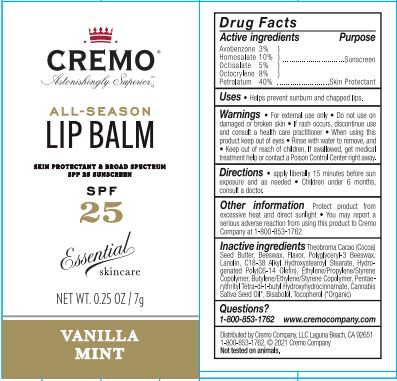 DRUG LABEL: Cremo All-Season Lip Balm SPF 25 Vanilla Mint
NDC: 71825-120 | Form: OINTMENT
Manufacturer: Cremo Company
Category: otc | Type: HUMAN OTC DRUG LABEL
Date: 20220106

ACTIVE INGREDIENTS: AVOBENZONE 3 g/1000 g; OCTISALATE 5 g/1000 g; HOMOSALATE 10 g/1000 g; PETROLATUM 40 g/1000 g; OCTOCRYLENE 8 g/1000 g
INACTIVE INGREDIENTS: C18-38 ALKYL HYDROXYSTEAROYL STEARATE; CANNABIS SATIVA SEED OIL; TOCOPHEROL; PENTAERYTHRITOL TETRAKIS(3-(3,5-DI-TERT-BUTYL-4-HYDROXYPHENYL)PROPIONATE); COCOA BUTTER; YELLOW WAX; LEVOMENOL; LANOLIN

Lip Balm SPF 25 Vanilla Mint

Active Ingredients

Avobenzone 3%

Homosalate 10%

Octisalate 5%

Octocrylene 8%

Petrolatum 40%

Purpose

Sunscreen

Skin Protectant

Uses

Helps Prevent sunburn and chapped lips.

Warnings

For external use only

Do not use on damaged or broken skin.

STOP USE

If rash occurs, discontinue use and consult a health care practitioner

When using this product keep out of eyes. Rinse with water to remove.

Keep out of reach of children.

If swallowed, get medical treatment help or contact a Poison Control Center right away.

Directions

Apply liberally 15 minutes before sun exposure and as needed. Children under 6 months, consult a doctor.

Inactive Ingredients

Theobroma Cacao (Cocoa) Seed Butter, Beeswax, Flavor, Polyglyceryl-3 Beeswax, Lanolin, C18-38 Alkyl Hydroxystearoyl Stearate, Hydrogenated Poly (C6-14 Olefin), Ethylene/Propylene/Styrene Copolymer, Butylene/Ethylene/Styrene Copolymer, Pentaerythrityl Tetra-di-t-butyl Hydroxyhydrocinnamate, Cannabis Sativa Seed Oil*, Bisabolol, Tocopherol.
*Organic

Other Information

Protect product from excessive heat and direct sunlight. You may report a serious adverse reaction from using this product to Cremo Company at 1-800-853-1762.

Questions?

1-800-853-1762 www.cremocompany.com

PACKAGE LABEL

Cremo All-Season Lip Balm SPF 25